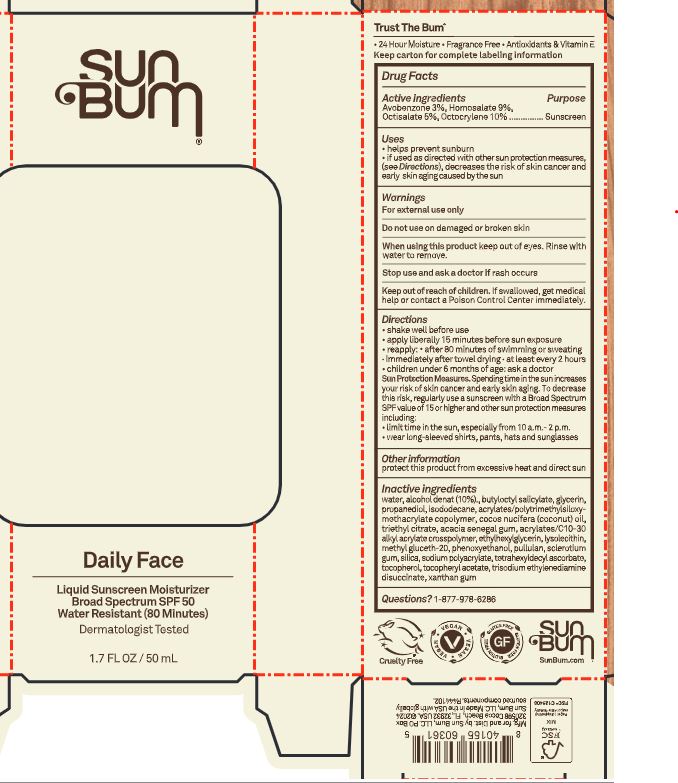 DRUG LABEL: Sun Bum Daily Face Liquid Sunscreen Moisturizer Broad Spectrum SPF 50
NDC: 69039-664 | Form: LOTION
Manufacturer: Sun Bum, LLC
Category: otc | Type: HUMAN OTC DRUG LABEL
Date: 20250923

ACTIVE INGREDIENTS: OCTISALATE 50 mg/1 mL; AVOBENZONE 30 mg/1 mL; HOMOSALATE 90 mg/1 mL; OCTOCRYLENE 100 mg/1 mL
INACTIVE INGREDIENTS: TETRAHEXYLDECYL ASCORBATE; GLYCERIN; BUTYLOCTYL SALICYLATE; ISODODECANE; .ALPHA.-TOCOPHEROL ACETATE; METHYL GLUCETH-20; COCOS NUCIFERA (COCONUT) OIL; ACACIA SENEGAL GUM; XANTHAN GUM; ALCOHOL; SILICA; WATER; PHENOXYETHANOL; TRISODIUM ETHYLENEDIAMINE DISUCCINATE; PROPANEDIOL; BUTYL ACRYLATE/METHYL METHACRYLATE/TRIMETHYLSILOXYMETHACRYLATE COPOLYMER; TOCOPHEROL; LYSOPHOSPHATIDYLCHOLINE, SOYBEAN; SCLEROTIUM GUM; PULLULAN; ACRYLATES/C10-30 ALKYL ACRYLATE CROSSPOLYMER (60000 MPA.S); ETHYLHEXYLGLYCERIN; TRIETHYL CITRATE; SODIUM POLYACRYLATE (2500000 MW)

Sun Bum Daily Face Liquid Sunscreen Moisturizer Broad Spectrum SPF 50

Active Ingredients

Avobenzone 3%, Homosalate 9%, Octisalate 5%, Octocrylene 10%

Purpose

Sunscreen

Uses

• helps prevent sunburn • if used as directed with other sun protection measures, (see Directions) decreases the risk of skin cancer and early skin aging caused by the sun

Warnings

For external use only

Do not use on damaged or broken skin

When using this product keep out of eyes. Rinse with water to remove.

Stop use and ask a doctor if rash occurs

Keep out of reach of children. If swallowed, get medical help or contact a Poison Control Center immediately.

Warnings

Keep Out Of Reach Of Children

Directions

• shake well before use

• apply liberally 15 minutes before sun exposure

• reapply: • after 80 minutes of swimming or sweating • immediately after towel drying • at least every 2 hours

• children under 6 months of age: ask a doctor

• Sun Protection Measures. Spending time in the sun increases your risk of skin cancer and early skin aging. To decrease this risk, regularly use a sunscreen with a Broad Spectrum SPF value of 15 or higher and other sun protection measures including:

• limit time in the sun, especially from 10 a.m.- 2 p.m.

• wear long-sleeved shirts, pants, hats and sunglasses

Directions

• shake well before use

• apply liberally 15 minutes before sun exposure

Other information

protect this product from excessive heat and direct sun

Inactive ingredients

water, alcohol denat (10%)., butyloctyl salicylate, glycerin, propanediol, isododecane, acrylates/polytrimethylsiloxy-methacrylate copolymer, cocos nucifera (coconut) oil, triethyl citrate, acacia senegal gum, acrylates/C10-30 alkyl acrylate crosspolymer, ethylhexylglycerin, lysolecithin, methyl gluceth-20, phenoxyethanol, pullulan, sclerotium gum, silica, sodium polyacrylate, tetrahexyldecyl ascorbate, tocopherol, tocopheryl acetate, trisodium ethylenediamine disuccinate, xanthan gum

Questions?

1-877-978-6286